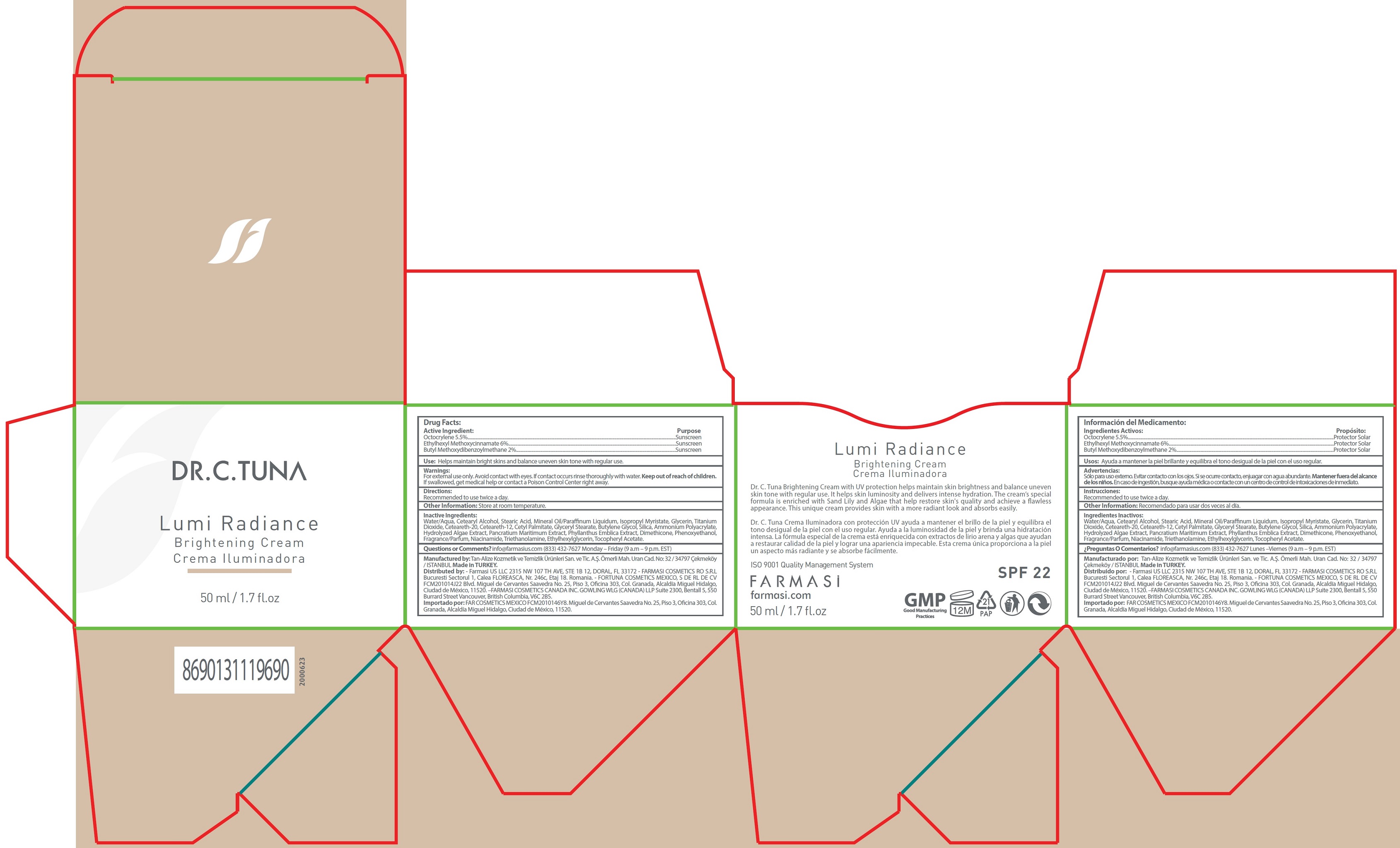 DRUG LABEL: Dr. C. Tuna Lumi Radiance Brightening Cream
NDC: 74690-013 | Form: CREAM
Manufacturer: Farmasi US LLC
Category: otc | Type: HUMAN OTC DRUG LABEL
Date: 20231105

ACTIVE INGREDIENTS: OCTOCRYLENE 55 mg/1 mL; OCTINOXATE 60 mg/1 mL; AVOBENZONE 20 mg/1 mL
INACTIVE INGREDIENTS: WATER; CETOSTEARYL ALCOHOL; STEARIC ACID; MINERAL OIL; ISOPROPYL MYRISTATE; GLYCERIN; TITANIUM DIOXIDE; POLYOXYL 20 CETOSTEARYL ETHER; CETEARETH-12; CETYL PALMITATE; GLYCERYL MONOSTEARATE; BUTYLENE GLYCOL; SILICON DIOXIDE; DIMETHICONE; PHENOXYETHANOL; NIACINAMIDE; TROLAMINE; ETHYLHEXYLGLYCERIN; .ALPHA.-TOCOPHEROL ACETATE

Dr. C. Tuna Lumi Radiance Brightening Cream

Active Ingredient:

Octocrylene 5.5% Ethylhexyl Methoxycinnamate 6% Butyl Methoxydibenzoylmethane 2%

Purpose

Sunscreen

Use:

Helps maintain bright skins and balance uneven skin tone with regular use.

Warnings:

For external use only. Avoid contact with eyes. If contact occurs rinse thoroughly with water.

Keep out of reach of children.

If swallowed, get medical help or contact a Poison Control Center right away.

Directions:

Recommended to use twice a day.

Other Information:

Store at room temperature.

Inactive Ingredients:

Water/Aqua, Cetearyl Alcohol, Stearic Acid, Mineral Oil/Paraffinum Liquidum, Isopropyl Myristate, Glycerin, Titanium Dioxide, Ceteareth-20, Ceteareth-12, Cetyl Palmitate, Glyceryl Stearate, Butylene Glycol, Silica, Ammonium Polyacrylate, Hydrolyzed Algae Extract, Pancratium Maritimum Extract, Phyllanthus Emblica Extract, Dimethicone, Phenoxyethanol, Fragrance/Parfum, Niacinamide, Triethanolamine, Ethylhexylglycerin, Tocopheryl Acetate.

Questions or Comments?

info@farmasius.com (833) 432-7627 Monday – Friday (9 a.m – 9 p.m. EST)